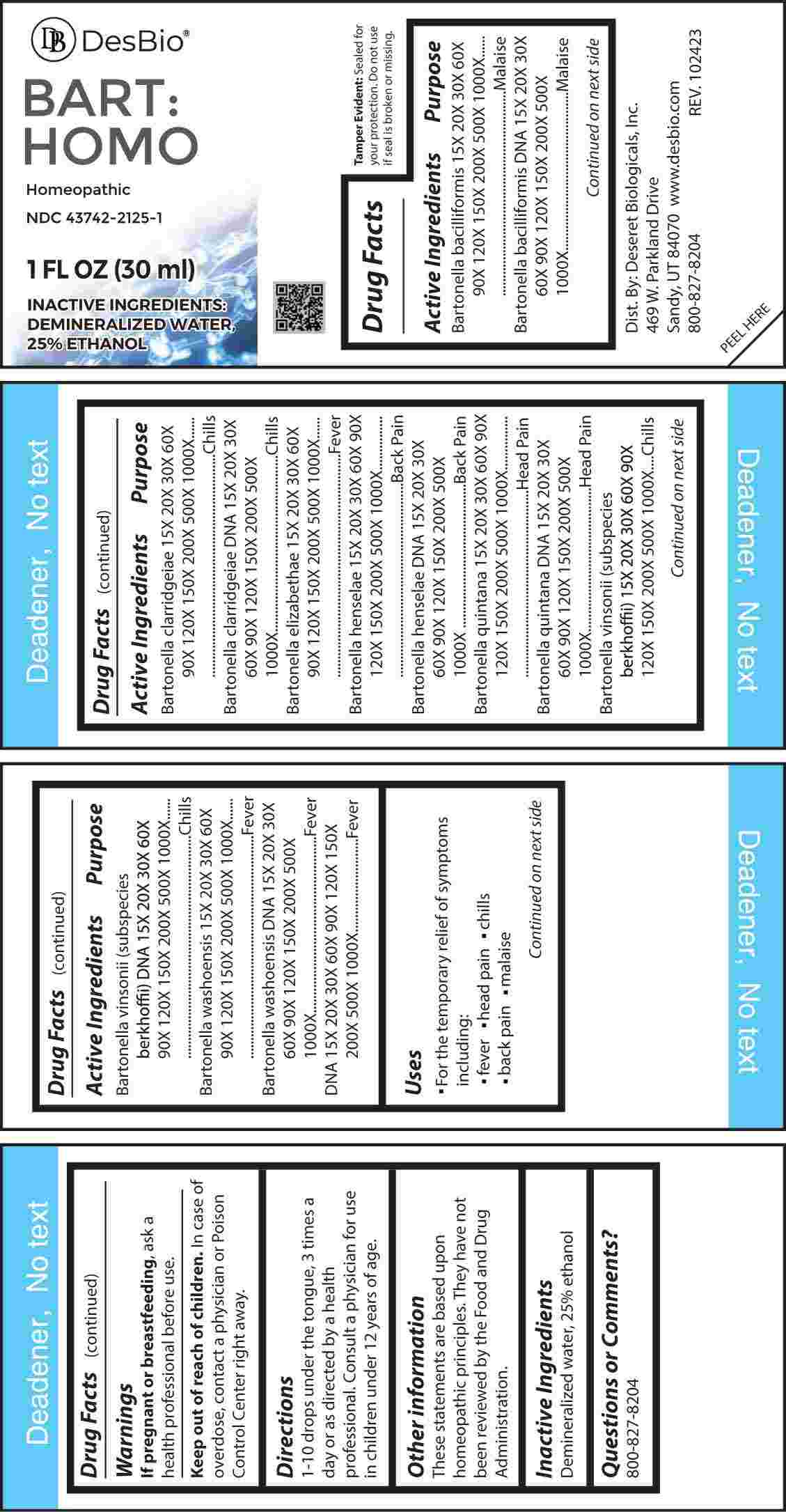 DRUG LABEL: Bart Homo
NDC: 43742-2125 | Form: LIQUID
Manufacturer: Deseret Biologicals, Inc.
Category: homeopathic | Type: HUMAN OTC DRUG LABEL
Date: 20240502

ACTIVE INGREDIENTS: BARTONELLA BACILLIFORMIS 15 [hp_X]/1 mL; BARTONELLA BACILLIFORMIS DNA 15 [hp_X]/1 mL; BARTONELLA CLARRIDGEIAE 15 [hp_X]/1 mL; BARTONELLA CLARRIDGEIAE DNA 15 [hp_X]/1 mL; BARTONELLA ELIZABETHAE 15 [hp_X]/1 mL; BARTONELLA HENSELAE 15 [hp_X]/1 mL; BARTONELLA HENSELAE DNA 15 [hp_X]/1 mL; BARTONELLA QUINTANA 15 [hp_X]/1 mL; BARTONELLA QUINTANA DNA 15 [hp_X]/1 mL; BARTONELLA VINSONII 15 [hp_X]/1 mL; BARTONELLA VINSONII DNA 15 [hp_X]/1 mL; BARTONELLA WASHOENSIS 15 [hp_X]/1 mL; BARTONELLA WASHOENSIS DNA 15 [hp_X]/1 mL; HERRING SPERM DNA 15 [hp_X]/1 mL
INACTIVE INGREDIENTS: WATER; ALCOHOL

DRUG FACTS:

ACTIVE INGREDIENTS:

Bartonella Bacilliformis 15X, 20X, 30X, 60X, 90X, 120X, 150X, 200X, 500X, 1000X, Bartonella Bacilliformis DNA 15X, 20X, 30X, 60X, 90X, 120X, 150X, 200X, 500X, 1000X, Bartonella Clarridgeiae 15X, 20X, 30X, 60X, 90X, 120X, 150X, 200X, 500X, 1000X, Bartonella Clarridgeiae DNA 15X, 20X, 30X, 60X, 90X, 120X, 150X, 200X, 500X, 1000X, Bartonella Elizabethae 15X, 20X, 30X, 60X, 90X, 120X, 150X, 200X, 500X, 1000X, Bartonella Henselae 15X, 20X, 30X, 60X, 90X, 120X, 150X, 200X, 500X, 1000X, Bartonella Henselae DNA 15X, 20X, 30X, 60X, 90X, 120X, 150X, 200X, 500X, 1000X, Bartonella Quintana 15X, 20X, 30X, 60X, 90X, 120X, 150X, 200X, 500X, 1000X, Bartonella Quintana DNA 15X, 20X, 30X, 60X, 90X, 120X, 150X, 200X, 500X, 1000X, Bartonella Vinsonii 15X, 20X, 30X, 60X, 90X, 120X, 150X, 200X, 500X, 1000X, Bartonella Vinsonii DNA 15X, 20X, 30X, 60X, 90X, 120X, 150X, 200X, 500X, 1000X, Bartonella Washoensis 15X, 20X, 30X, 60X, 90X, 120X, 150X, 200X, 500X, 1000X, Bartonella Washoensis DNA 15X, 20X, 30X, 60X, 90X, 120X, 150X, 200X, 500X, 1000X, DNA 15X, 20X, 30X, 60X, 90X, 120X, 150X, 200X, 500X, 1000X.

PURPOSE:

Bartonella Bacilliformis - Malaise, Bartonella Bacilliformis DNA - Malaise, Bartonella Clarridgeiae - Chill, Bartonella Clarridgeiae DNA - Chill, Bartonella Elizabethae - Fever, Bartonella Henselae – Back Pain, Bartonella Henselae DNA – Back Pain, Bartonella Quintana – Head Pain, Bartonella Quintana DNA – Head Pain, Bartonella Vinsonii - Chills, Bartonella Vinsonii DNA - Chills, Bartonella Washoensis – Fever, Bartonella Washoensis DNA – Fever, DNA - Fever

USES:

• For the temporary relief of symptoms including:

• fever • head pain • chills • back pain • malaise

These statements are based upon homeopathic principles. They have not been reviewed by the Food and Drug Administration.

WARNINGS:

If pregnant or breast-feeding, ask a health professional before use.

Keep out of reach of children. In case of overdose, contact a physician or Poison Control Center right away.

Tamper Evident: Sealed for your protection. Do not use if seal is broken or missing.

KEEP OUT OF REACH OF CHILDREN:

In case of overdose, contact a physician or Poison Control Center right away.

DIRECTIONS:

1-10 drops under the tongue, 3 times a day or as directed by a health professional. Consult a physician for use in children under 12 years of age.

INACTIVE INGREDIENTS:

Demineralized water, 25% ethanol

QUESTIONS:

Dist. By: Deseret Biologicals, Inc.
469 W. Parkland Drive
Sandy, UT 84070 www.desbio.com

800-827-8204

PACKAGE LABEL DISPLAY:

DesBio

BART:

HOMO

Homeopathic

NDC 43742-2125-1

1 FL OZ (30 ml)